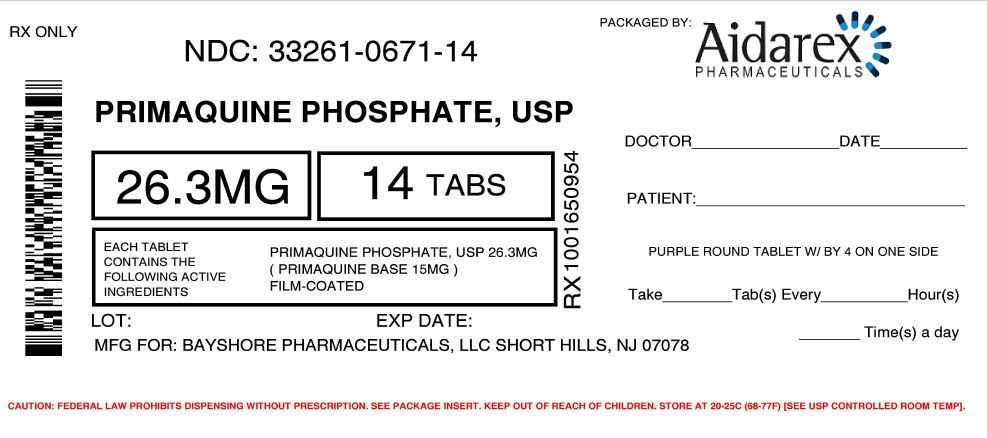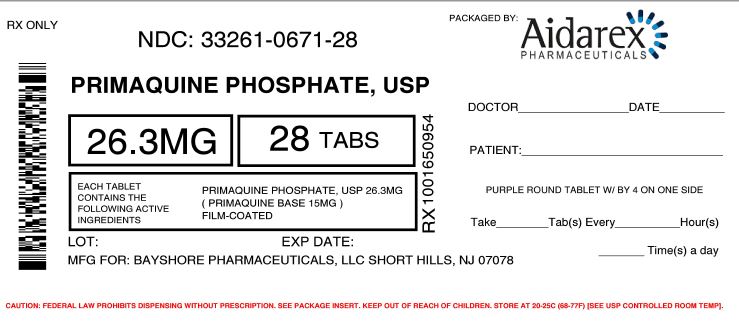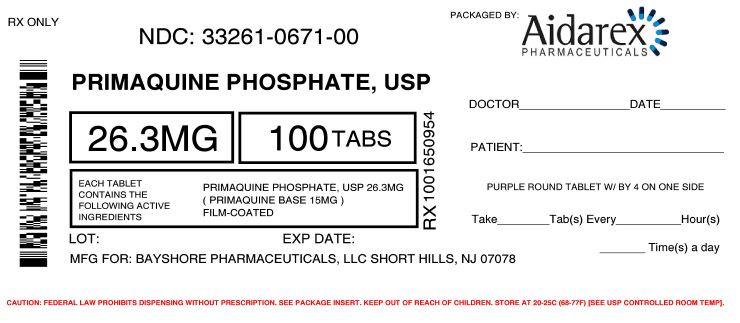 DRUG LABEL: Primaquine Phosphate
NDC: 33261-671 | Form: TABLET
Manufacturer: Aidarex Pharmaceuticals LLC
Category: prescription | Type: HUMAN PRESCRIPTION DRUG LABEL
Date: 20170719

ACTIVE INGREDIENTS: PRIMAQUINE PHOSPHATE 15 mg/1 1
INACTIVE INGREDIENTS: CELLULOSE, MICROCRYSTALLINE; STARCH, CORN; LACTOSE MONOHYDRATE; MAGNESIUM STEARATE; WATER; HYPROMELLOSES; TITANIUM DIOXIDE; POLYETHYLENE GLYCOLS; FD&C RED NO. 40; FD&C BLUE NO. 2

PRIMAQUINE
PHOSPHATE
TABLETS, USP

WARNING

PHYSICIANS SHOULD COMPLETELY FAMILIARIZE THEMSELVES WITH THE COMPLETE CONTENTS OF THIS LEAFLET BEFORE PRESCRIBING PRIMAQUINE PHOSPHATE.

DESCRIPTION

Primaquine phosphate is 8-[(4-Amino-1-methylbutyl)amino]-6-methoxyquinoline phosphate, a synthetic compound with potent antimalarial activity. Each tablet contains 26.3 mg of Primaquine phosphate (equivalent to 15 mg of primaquine base). The dosage is customarily expressed in terms of the base.

Inactive Ingredients: Microcrystalline Cellulose, Pregelatinized Starch, Lactose Monohydrate, Magnesium Stearate, Purified water, Hypromellose, Opadry Purple, Titanium Dioxide, Macrgol/PEG, FD&C Red #40 and FD&C Blue #2.

CLINICAL PHARMACOLOGY

Primaquine phosphate is an 8-aminoquinoline compound which eliminates tissue (exoerythrocytic) infection. Thereby, it prevents the development of the blood (erythrocytic) forms of the parasite which are responsible for relapses in vivax malaria. Primaquine phosphate is also active against gametocytes of Plasmodium falciparum.

INDICATIONS AND USAGE

Primaquine phosphate is indicated for the radical cure (prevention of relapse) of vivax malaria.

CONTRAINDICATIONS

Primaquine phosphate is contraindicated in acutely ill patients suffering from systemic disease manifested by tendency to granulocytopenia, such as rheumatoid arthritis and lupus erythematosus. The drug is also contraindicated in patients receiving concurrently other potentially hemolytic drugs or depressants of myeloid elements of the bone marrow.

Because quinacrine hydrochloride appears to potentiate the toxicity of antimalarial compounds which are structurally related to primaquine, the use of quinacrine in patients receiving primaquine is contraindicated. Similarly, Primaquine should not be administered to patients who have received quinacrine recently, as toxicity is increased.

WARNINGS

Discontinue the use of Primaquine phosphate promptly if signs suggestive of hemolytic anemia occur (darkening of the urine, marked fall of hemoglobin or erythrocytic count).

Hemolytic reactions (moderate to severe) may occur in individuals with glucose-6-phosphate dehydrogenase (G-6-PD) deficiency and in individuals with a family or personal history of favism. Areas of high prevalence of G-6-PD deficiency are Africa, Southern Europe, Mediterranean region, Middle East, South-East Asia, and Oceania. People from these regions have a greater tendency to develop hemolytic anemia (due to a congenital deficiency of erythrocytic glucose-6-phosphate dehydrogenase) while receiving Primaquine and related drugs.

Usage in Pregnancy

Safe usage of this preparation in pregnancy has not been established. Therefore, use of it during pregnancy should be avoided except when in the judgment of the physician the benefit outweighs the possible hazard.

PRECAUTIONS

Since anemia, methemoglobinemia, and leukopenia have been observed following administration of large doses of primaquine, the adult dosage of 1 tablet (= 15 mg base) daily for fourteen days should not be exceeded. It is also advisable to make routine blood examinations (particularly blood cell counts and hemoglobin determinations) during therapy.

If primaquine phosphate is prescribed for (1) an individual who has shown a previous idiosyncrasy to primaquine phosphate (as manifested by hemolytic anemia, methemoglobinemia, or leukopenia), (2) an individual with a family or personal history of favism, or (3) an individual with erythrocytic glucose-6-phosphate dehydrogenase (G-6-PD) deficiency or nicotinamide adenine dinucleotide (NADH) methemoglobin reductase deficiency, the person should be observed closely for tolerance. The drug should be discontinued immediately if marked darkening of the urine or sudden decrease in hemoglobin concentration or leukocyte count occurs.

Due to potential for QT interval prolongation, monitor ECG when using Primaquine in patients with cardiac disease, long QT syndrome, a history of ventricular arrhythmias, uncorrected hypokalemia and/or hypomagnesemia, or bradycardia (<50 bpm), and during concomitant administration with QT interval prolonging agents (see PRECAUTIONS, Drug Interactions, ADVERSE REACTIONS, and OVERDOSAGE).

Drug Interactions

Caution is advised if Primaquine is used concomitantly with other drugs that prolong the QT interval (see PRECAUTIONS, ADVERSE REACTIONS, and OVERDOSAGE).

Geriatric Use

Clinical studies of Primaquine did not include sufficient numbers of subjects aged 65 and over to determine whether they respond differently from younger subjects. Other reported clinical experience has not identified differences in responses between the elderly and younger patients. In general, dose selection for an elderly patient should be cautious, usually starting at the low end of the dosing range, reflecting the greater frequency of decreased hepatic, renal, or cardiac function, and of concomitant disease or other drug therapy.

ADVERSE REACTIONS

Gastrointestinal: nausea, vomiting, epigastric distress, and abdominal cramps.

Hematologic: leukopenia, hemolytic anemia in glucose-6-phosphate dehydrogenase (G-6-PD) deficient individuals, and methemoglobinemia in nicotinamide adenine dinucleotide (NADH) methemoglobin reductase deficient individuals.

Cardiac: Cardiac Arrhythmia and QT interval prolongation (see PRECAUTIONS, OVERDOSAGE).

OVERDOSAGE

Symptoms of overdosage of primaquine phosphate include abdominal cramps, vomiting, burning epigastric distress, central nervous system and cardiovascular disturbances, including cardiac arrhythmia and QT interval prolongation, cyanosis, methemoglobinemia, moderate leukocytosis or leukopenia, and anemia. The most striking symptoms are granulocytopenia and acute hemolytic anemia in sensitive persons. Acute hemolysis occurs, but patients recover completely if the dosage is discontinued.

DOSAGE AND ADMINISTRATION

Primaquine phosphate is recommended only for the radical cure of vivax malaria, the prevention of relapse in vivax malaria, or following the termination of chloroquine phosphate suppressive therapy in an area where vivax malaria is endemic. Patients suffering from an attack of vivax malaria or having parasitized red blood cells should receive a course of chloroquine phosphate, which quickly destroys the erythrocytic parasites and terminates the paroxysm. Primaquine phosphate should be administered concurrently in order to eradicate the exoerythrocytic parasites in a dosage of 1 tablet (equivalent to 15 mg base) daily for 14 days.

HOW SUPPLIED

Primaquine Phosphate USP Tablets are solid oral formulation round tablet debossed "BY4" available in 26.3 mg and 14, 28, and 100 count.

Available in bottles of 100. (NDC 33261-0671-14)

Available in bottles of 100. (NDC 33261-0671-28)

Available in bottles of 100. (NDC 33261-0671-00)

STORAGE AND HANDLING

Store at controlled room temperature: 25°C (77°F); excursions are permitted to 15°-30°C (59°-86°F) [see USP Controlled Room Temperature].

Dispense in tight, light-resistant container as defined in the USP/NF.

Clinical Studies

Persons with acute attacks of vivax malaria, provoked by the release of erythrocytic forms of the parasite, respond readily to therapy, particularly to Chloroquine Phosphate. Primaquine eliminates tissue (exoerythrocytic) infection and prevents relapses in experimentally induced vivax malaria in human volunteers and in persons with naturally occurring infections and is a valuable adjunct to conventional therapy in vivax malaria.

Call your doctor for medical advice about side effects. You may report side effects to FDA at 1-800- FDA1088.

Rx Only

Manufactured for:

Bayshore Pharmaceuticals LLC
Short Hills, NJ 07078
1-800-593-5725

Repackaged By:

Aidarex Pharmaceuticals, LLC

Corona, CA 92882

Revised 10/2015

PRINCIPAL DISPLAY PANEL - 26.3 mg Tablet Bottle Label

NDC 76385-102-01
Primaquine phosphate Tablets, USP
26.3 mg (=15 mg base)

Rx only

100 Tablets

Adult dosage should not exceed 1 tablet daily for 14 days.

Discontinue promptly if signs suggestive of hemolytic anemia occur (i.e., darkening of urine, marked fall of hemoglobin, or erythrocyte count). Usual Dosage: See package insert.

Dispense in tight, light-resistant container as defined in the USP/NF. Store at 25° C (77° F); excursions permitted to 15° C-30° C (59° F-86° F) [see USP Controlled Room Temperature].

Manufactured for: Bayshore Pharmaceuticals LLC
Short Hills, NJ 07078